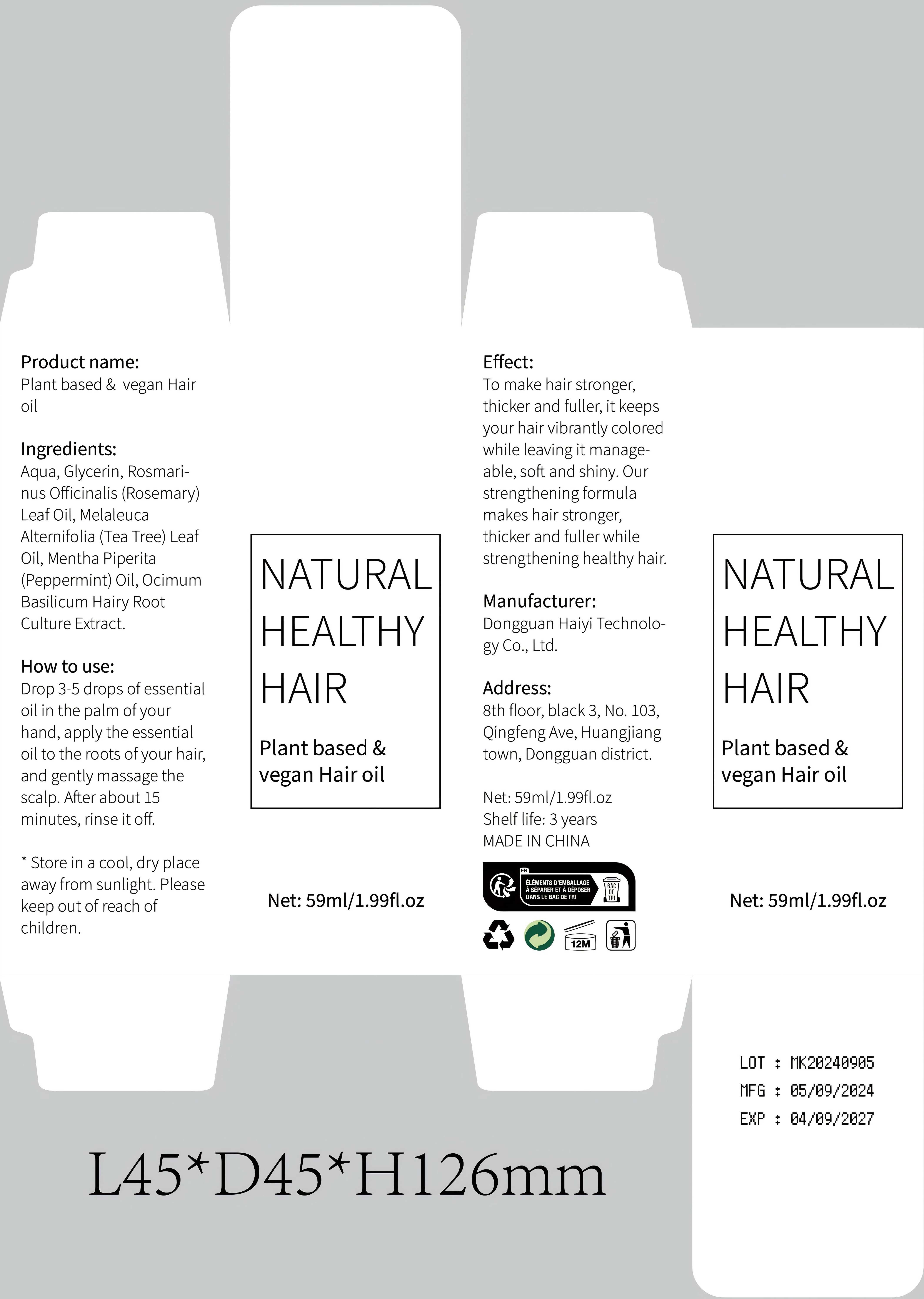 DRUG LABEL: Plant based  vegan Hair oil
NDC: 84732-048 | Form: OIL
Manufacturer: Dongguan Haiyi Technology Co.,Ltd.
Category: otc | Type: HUMAN OTC DRUG LABEL
Date: 20241016

ACTIVE INGREDIENTS: OCIMUM BASILICUM ROOT 1 mg/100 mL
INACTIVE INGREDIENTS: WATER; MELALEUCA ALTERNIFOLIA (TEA TREE) LEAF OIL; PEPPERMINT OIL; GLYCERIN; ROSEMARY OIL

Active ingredient

Ocimum Basilicum Hairy Root Culture Extract.

Inactive ingredient

Aqua, Glycerin, Rosmarinus Officinalis (Rosemary) Leaf Oil, Melaleuca Alternifolia (Tea Tree) Leaf Oil, Mentha Piperita (Peppermint) Oil

Purpose section

To make hair stronger,thicker and fuller, it keepsyour hair vibrantly coloredwhile leaving it manage-able, soft and shiny.Our strengthening formula makes hair stronger,thicker and fuller while strengthening healthy hair.

Warning

1).For external use only, avoid directcontact with eyes, lf you feel any discomfort, stop using itand wash it with plenty of water. In severe cases, pleaseseek medical attention in time.
2). Not allowed to be used ondamaged skin,

stop use

This product may cause allergic reactions in asmall number of people.
lf you experience any discomfort,please stop using it immediately.

not use

Not suitable for use by children, pregnantor breast feeding people.

OUT OF CHILDREN

KEEP THE PRODUCT OUT OF REACH OF CHILDREN to

HOW TO USE

Drop 3-5 drops of essentialoil in the palm ofyourhand, apply the essentialoil to the roots of your hair,and gently massage thescalp. After about 15minutes, rinse it off.

Dosage

take an appropriateamount,Use 2-3 times a week